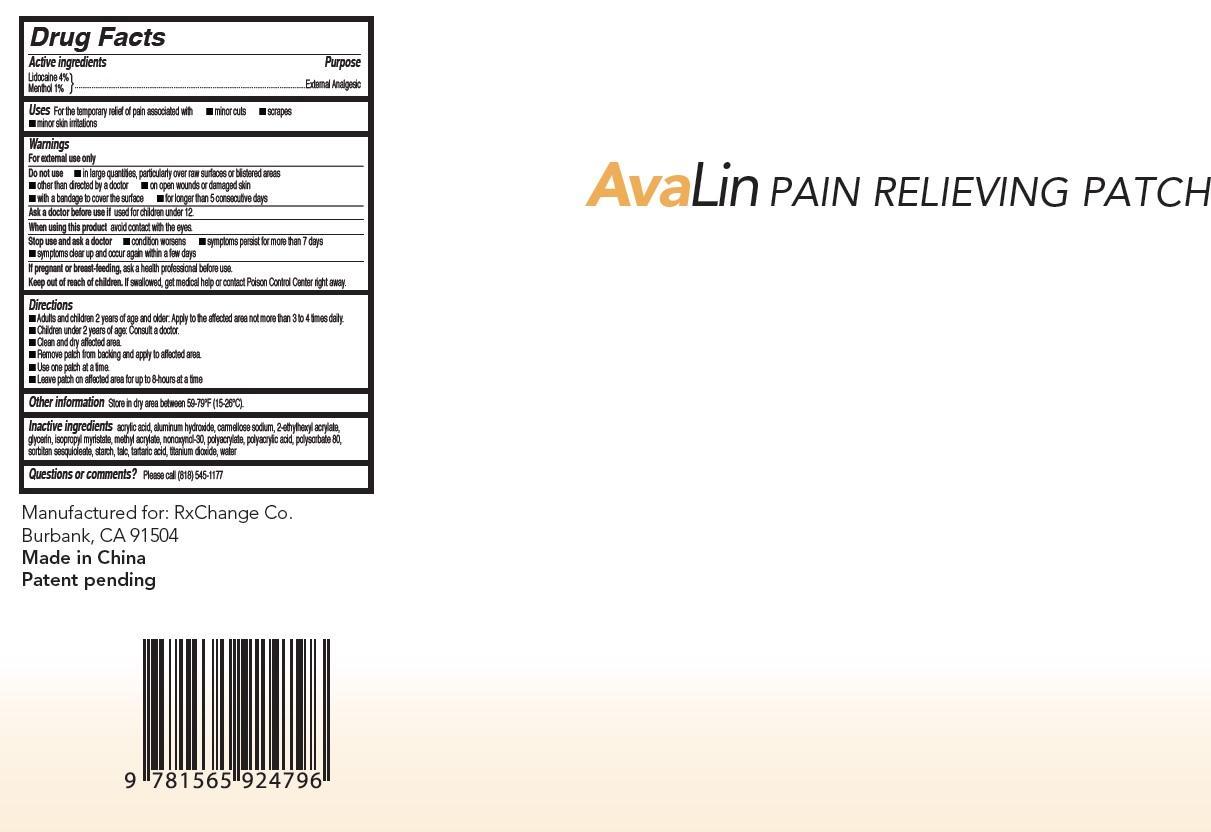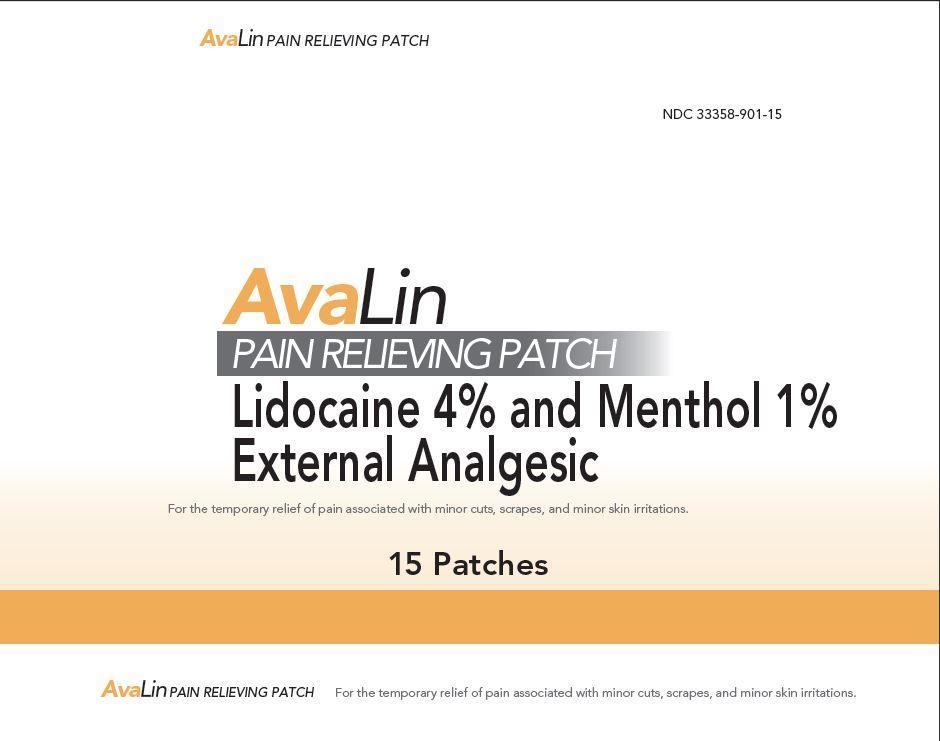 DRUG LABEL: Avalin External Analgesic Patch
NDC: 33358-901 | Form: PATCH
Manufacturer: RxChange Co.
Category: otc | Type: HUMAN OTC DRUG LABEL
Date: 20150129

ACTIVE INGREDIENTS: LIDOCAINE 40 mg/1 g; MENTHOL 10 mg/1 g
INACTIVE INGREDIENTS: ACRYLIC ACID; ALUMINUM HYDROXIDE; CROSCARMELLOSE SODIUM; 2-ETHYLHEXYL ACRYLATE; GLYCERIN; ISOPROPYL MYRISTATE; METHYL ACRYLATE; NONOXYNOL-30; POLYSORBATE 80; SORBITAN SESQUIOLEATE; TALC; TARTARIC ACID; TITANIUM DIOXIDE; WATER

Avalin External Analgesic Patch

Active ingredients

Lidocaine 4%

Menthol 1%

Purpose

External Analgesic

Uses

For the temporary relief pain associated with • minor cuts • scrapes • minor skin imitations

Warnings

For external use only

Do not use

• in large quantities, particularly over raw surfaces or blistered areas

• other than directed by a doctor • on open wounds or damaged skin

• with a bandage to cover the surface • for longer than 5 consecutive days

Ask a doctor before use

if used for children under 12.

When using this product

avoid contact with the eyes.

Stop use and ask a doctor

• condition worsens • symptoms persist for more than 7 days

• symptoms clear up and occur again within a few days

If pregnant or breast-feeding, ask a health professional before use.

Keep out of reach of children.

If swallowed, get a medical help or contact Poison Control Center right away.

Directions

- Adults and children 2 years of age and older: Apply to the affected area not more than 3 to 4 times daily.
- Children under 2 years of age: Consult a doctor.
- Clean and dry affected area.
- Remove patch from backing and apply to affected area.
- Use one patch at a time.
- Leave patch on affected area for up to 8-hours at a time

Other information

Store in dry area between 59-79 F(15-26 C)

Inactive ingredients

acrylic acid, aluminum hydroxide, carmellose sodium, 2-ethylhexyl acrylate, glycerin, isopropyl myristate, methyl acrylate, nonoxynol-30, polyacrylate, polyacrylic acid, polysorbate 80, sorbitan sesquioleate, starch, talc, tartaric acid, titanium dioxide, water

Questions or comments?

Please call (818) 545-1177